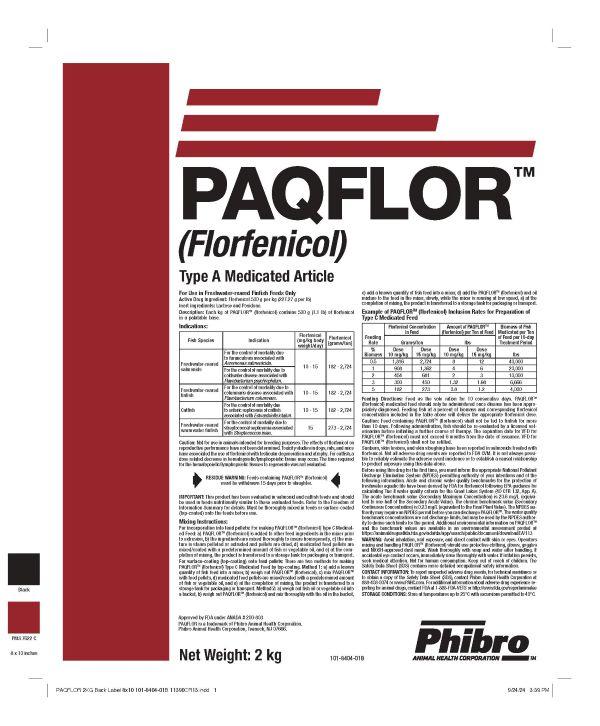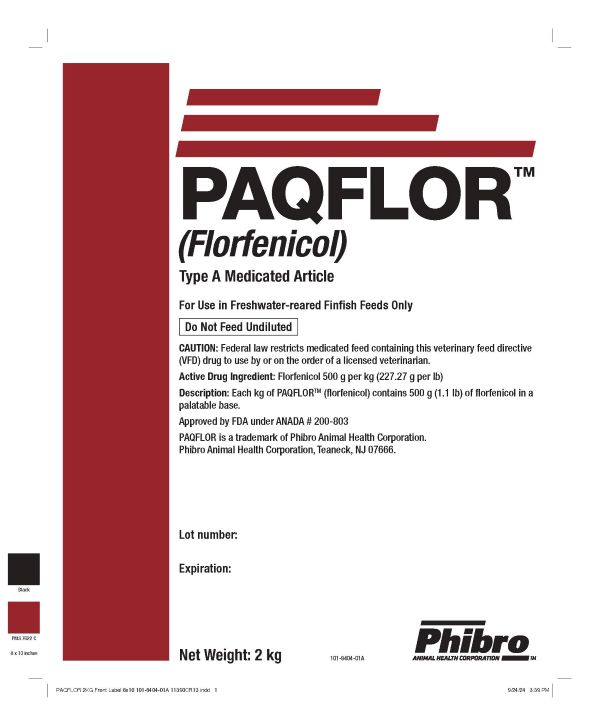 DRUG LABEL: PAQFLOR
NDC: 66104-8101 | Form: POWDER
Manufacturer: Phibro Animal Health
Category: animal | Type: VFD TYPE A MEDICATED ARTICLE ANIMAL DRUG LABEL
Date: 20250325

ACTIVE INGREDIENTS: FLORFENICOL 500 g/1 kg

PAQFLORTM
(Florfenicol)
Type A Medicated Article

PAQFLORTM (Florfenicol) Type A Medicated Article

Active Drug Ingredient: Florfenicol 500 g per kg (227.27 g per lb)
Description: Each kg of PAQFLORTM (florfenicol) contains 500 g (1.1 lb) of florfenicol in a
palatable base.
Approved by FDA under ANADA # 200-803
PAQFLOR is a trademark of Phibro Animal Health Corporation.
Phibro Animal Health Corporation, Teaneck, NJ 07666.

Lot number:

Expiration:

Net Weight: 2 kg

101-8404-01A

For Use in Freshwater-reared Finfish Feeds Only Do Not Feed Undiluted

CAUTION: Federal law restricts medicated feed containing this veterinary feed directive
(VFD) drug to use by or on the order of a licensed veterinarian.

For Use in Freshwater-reared Finfish Feeds Only Active Drug Ingredient: Florfenicol 500 g per kg (227.27 g per lb) Inert ingredients: Lactose and Povidone. Description: Each kg of PAQFLORTM (florfenicol) contains 500 g (1.1 lb) of florfenicol in a palatable base.

Indications:

Fish Species | Indication | Florefenicol; (mg/kg body; weight/day) | Florefenicol; (grams/ton)
Freshwater-reared salmonids | For the control of mortality due to furunculosis associated with Aeromonas salmonicida. | 10-15 | 182-2,724
 | For the control of mortality due to coldwater disease associated with Flavobacterium psychrophilum. | 10-15 | 182-2,724
Freshwater-reared finfish | For the control of mortality due to columnaris disease associated with Flavobacterium columnare. | 10-15 | 182-2,724
Catfish | For the control of mortality due to enteric septicemia of catfish associated with Edwardsiella ictaluri. | 10-15 | 182-2,724
Freshwater-reared warmwater finfish | For the control of mortality due to streptococcal septicemia associated with Streptococcus iniae. | 15 | 273-2,724

Caution: Not for use in animals intended for breeding purposes. The effects of florfenicol on
reproductive performance have not been determined. Toxicity studies in dogs, rats, and mice
have associated the use of florfenicol with testicular degeneration and atrophy. For catfish, a
dose related decrease in hematopoietic/lymphopoietic tissue may occur. The time required
for the hematopoietic/lymphopoietic tissues to regenerate was not evaluated.

RESIDUE WARNING: Feeds containing PAQFLORTM (florfenicol) must be withdrawn 15 days prior to slaughter.

IMPORTANT: This product has been evaluated in salmonid and catfish feeds and should
be used in feeds nutritionally similar to these evaluated feeds. Refer to the Freedom of
Information Summary for details. Must be thoroughly mixed in feeds or surface-coated
(top-coated) onto the feeds before use.

Mixing Instructions: For incorporation into feed pellets: For making PAQFLORTM (florfenicol) Type C Medicated
Feed: a) PAQFLORTM (florfenicol) is added to other feed ingredients in the mixer prior
to extrusion, b) the ingredients are mixed thoroughly to insure homogeneity, c) the mixture
is steam pelleted or extruded and pellets are dried, d) medicated feed pellets are
mixed/coated with a predetermined amount of fish or vegetable oil, and e) at the completion
of mixing, the product is transferred to a storage tank for packaging or transport.

For surface-coating (top-coating) onto feed pellets: There are two methods for making
PAQFLORTM (florfenicol) Type C Medicated Feed by top-coating. Method 1: a) add a known
quantity of fish feed into a mixer, b) weigh out PAQFLORTM (florfenicol), c) mix PAQFLORTM
with feed pellets, d) medicated feed pellets are mixed/coated with a predetermined amount
of fish or vegetable oil, and e) at the completion of mixing, the product is transferred to a
storage tank for packaging or transport. Method 2: a) weigh out fish oil or vegetable oil into
a bucket, b) weigh out PAQFLORTM (florfenicol) and mix thoroughly with the oil in the bucket,

c) add a known quantity of fish feed into a mixer, d) add the PAQFLORTM (florfenicol) and oil

mixture to the feed in the mixer, slowly, while the mixer is running at low speed, e) at the
completion of mixing, the product is transferred to a storage tank for packaging or transport.

Example of PAQFLORTM (florfenicol) Inclusion Rates for Preparation of Type C Medicated Feed

Feeding; Rate | Florfenicol Concentration; in Feed |  | Amount of PAQFLORTM; (florfenicol per Ton of Feed) |  | Biomass of Fish Medicated per Ton; of Feed per 10-day; Treatment Period
 | Grams/ton |  | lbs
%; Biomass | Dose; 10 mg/kg | Dose; 15 mg/kg | Dose; 10 mg/kg | Dose; 15 mg/kg | lbs
0.5 | 1,816 | 2,724 | 8 | 12 | 40,000
1 | 908 | 1,362 | 4 | 6 | 20,000
2 | 454 | 681 | 2 | 3 | 10,000
3 | 300 | 450 | 1.32 | 1.98 | 6,666
5 | 182 | 273 | 0.8 | 1.2 | 4,000

Feeding Directions: Feed as the sole ration for 10 consecutive days. PAQFLORTM
(florfenicol) medicated feed should only be administered once disease has been appropriately
diagnosed. Feeding fish at a percent of biomass and corresponding florfenicol
concentration included in the table above will deliver the appropriate florfenicol dose.

WARNINGS AND PRECAUTIONS

Caution: Feed containing PAQFLORTM (florfenicol) shall not be fed to finfish for more
than 10 days. Following administration, fish should be re-evaluated by a licensed veterinarian
before initiating a further course of therapy. The expiration date for VFD for
PAQFLORTM (florfenicol) must not exceed 6 months from the date of issuance. VFD for
PAQFLORTM (florfenicol) shall not be refilled.

Sunburn, skin lesions, and skin sloughing have been reported in salmonids treated with
florfenicol. Not all adverse drug events are reported to FDA CVM. It is not always possible
to reliably estimate the adverse event incidence or to establish a causal relationship
to product exposure using this data alone.

Before using this drug for the first time, you must inform the appropriate National Pollutant
Discharge Elimination System (NPDES) permitting authority of your intentions and of the
following information. Acute and chronic water quality benchmarks for the protection of
freshwater aquatic life have been derived by FDA for florfenicol following EPA guidance for
calculating Tier II water quality criteria for the Great Lakes System (40 CFR 132, App. A).
The acute benchmark value (Secondary Maximum Concentration) is 20.6 mg/L (equivalent
to one-half of the Secondary Acute Value). The chronic benchmark value (Secondary
Continuous Concentration) is 0.23 mg/L (equivalent to the Final Plant Value). The NPDES authority
may require an NPDES permit before you can discharge PAQFLORTM. The water quality
benchmark concentrations are not discharge limits, but may be used by the NPDES authority
to derive such limits for the permit. Additional environmental information on PAQFLORTM
and the benchmark values are available in an environmental assessment posted at
https://animaldrugsatfda.fda.gov/adafda/app/search/public/document/downloadEA/113

WARNINGS

WARNING: Avoid inhalation, oral exposure, and direct contact with skin or eyes. Operators
mixing and handling PAQFLORTM (florfenicol) should use protective clothing, gloves, goggles
and NIOSH-approved dust mask. Wash thoroughly with soap and water after handling. If
accidental eye contact occurs, immediately rinse thoroughly with water. If irritation persists,
seek medical attention. Not for human consumption. Keep out of reach of children. The
Safety Data Sheet (SDS) contains more detailed occupational safety information.

CONTACT INFORMATION: To report suspected adverse drug events, for technical assistance or
to obtain a copy of the Safety Data Sheet (SDS), contact Phibro Animal Health Corporation at
888-403-0074 or www.PAHC.com. For additional information about adverse drug experience reporting
for animal drugs, contact FDA at 1-888-FDA-VETS or http://www.fda.gov/reportanimalae

Approved by FDA under ANADA # 200-803
PAQFLOR is a trademark of Phibro Animal Health Corporation.
Phibro Animal Health Corporation, Teaneck, NJ 07666.

Net Weight: 2kg

101-8404-01B

STORAGE AND HANDLING

STORAGE CONDITIONS: Store at temperatures up to 25°C with excursions permitted to 40°C.

Label

PAQFLOR Front and Back Label